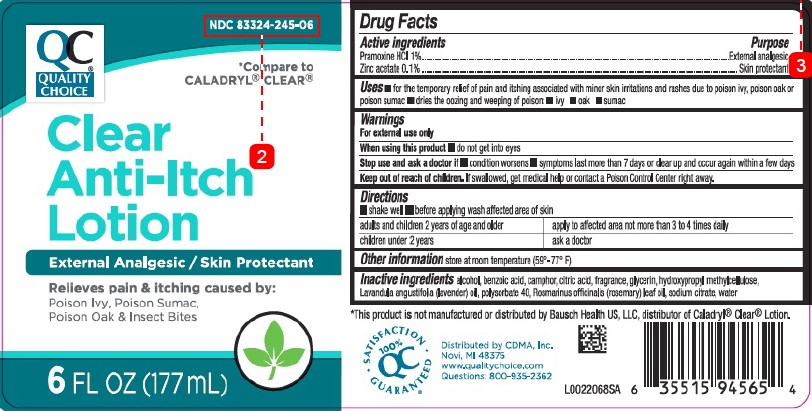 DRUG LABEL: Clear Anti-Itch
NDC: 83324-245 | Form: LOTION
Manufacturer: Chain Drug Marketing Association
Category: otc | Type: HUMAN OTC DRUG LABEL
Date: 20260227

ACTIVE INGREDIENTS: PRAMOXINE HYDROCHLORIDE 10 mg/1 mL; ZINC ACETATE 1 mg/1 mL
INACTIVE INGREDIENTS: ALCOHOL; BENZOIC ACID; CAMPHOR (SYNTHETIC); CITRIC ACID MONOHYDRATE; GLYCERIN; HYPROMELLOSE, UNSPECIFIED; LAVENDER OIL; POLYSORBATE 40; ROSEMARY OIL; SODIUM CITRATE; WATER

Quality Choice 218.002/218AF
Clear Anti-Itch Lotion

Active ingredients

Pramoxine HCl 1%
Zinc acetate 0.1%

Purpose

External analgesic
Skin protectant

Uses

- for the temporary relief of pain and itching associated with minor skin irritations and rashes due to poison ivy, poison oak, or poison sumac
- dries the oozing and weeping of poison: -ivy -oak -sumac

Warnings

For external use only

When using this product

•do not get into eyes

Stop use and ask a doctor if

•condition worsens •symptoms last more than 7 days or clear up and occur again within a few days

Keep out of reach of children.

If swallowed, get medical help or contact a Poison Control Center right away.

Directions

- shake well
- before applying wash affected area of skin

adults and children 2 years of age and older - apply to affected area no more than 3 to 4 times daily

children under 2 years - ask a doctor

Other information

store at room temperature (59⁰ - 77⁰ F)

Inactive ingredients

alcohol, benzoic acid, camphor, citric acid, fragrance, glycerin, hydroxypropyl methylcellulose, Lavandula angustifolia (lavender) oil, polysorbate 40, Rosmarinus officinalis (rosemary) leaf oil, sodium citrate, water

Disclaimer

*This product is not manufactured or distributed by Bausch Health US, LLC, distributor of Caladryl Clear Lotion.

ADVERSE REACTION

Distibuted by CDMA, Inc.

Novi, MI 48375

www.qualitychoice.com

Questions: 800-935-2362

SATISFACTION GUARANTEED

100% QC

PRINCIPAL DISPLAY PANEL

NDC 83324-245-06

QC

QUALITY CHOICE

*Compare to CALADRYL CLEAR

Clear

Anti-Itch

Lotion

External Analgesic/Skin Protectant

Relieves pain & itching caused by:

Poison Ivy, Poison Sumac, Poison Oak & Insect Bites

6 FL OZ (177 mL)